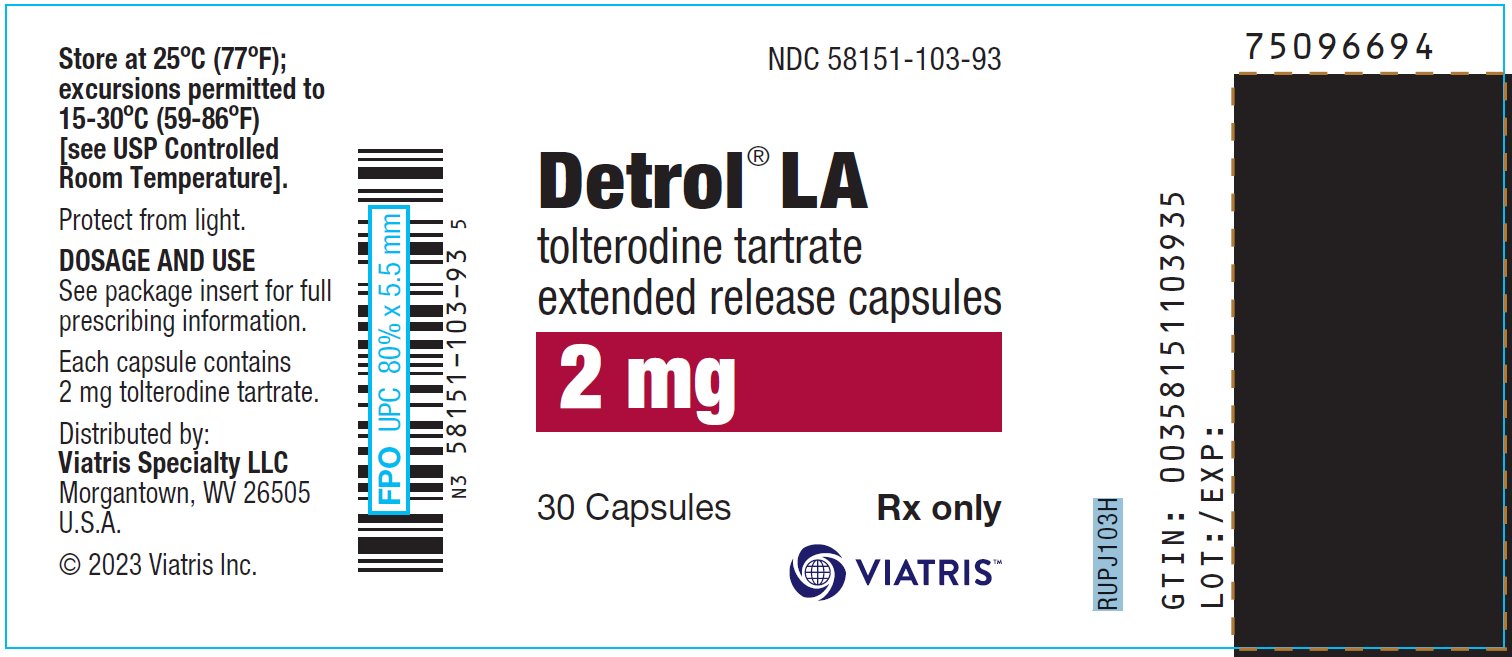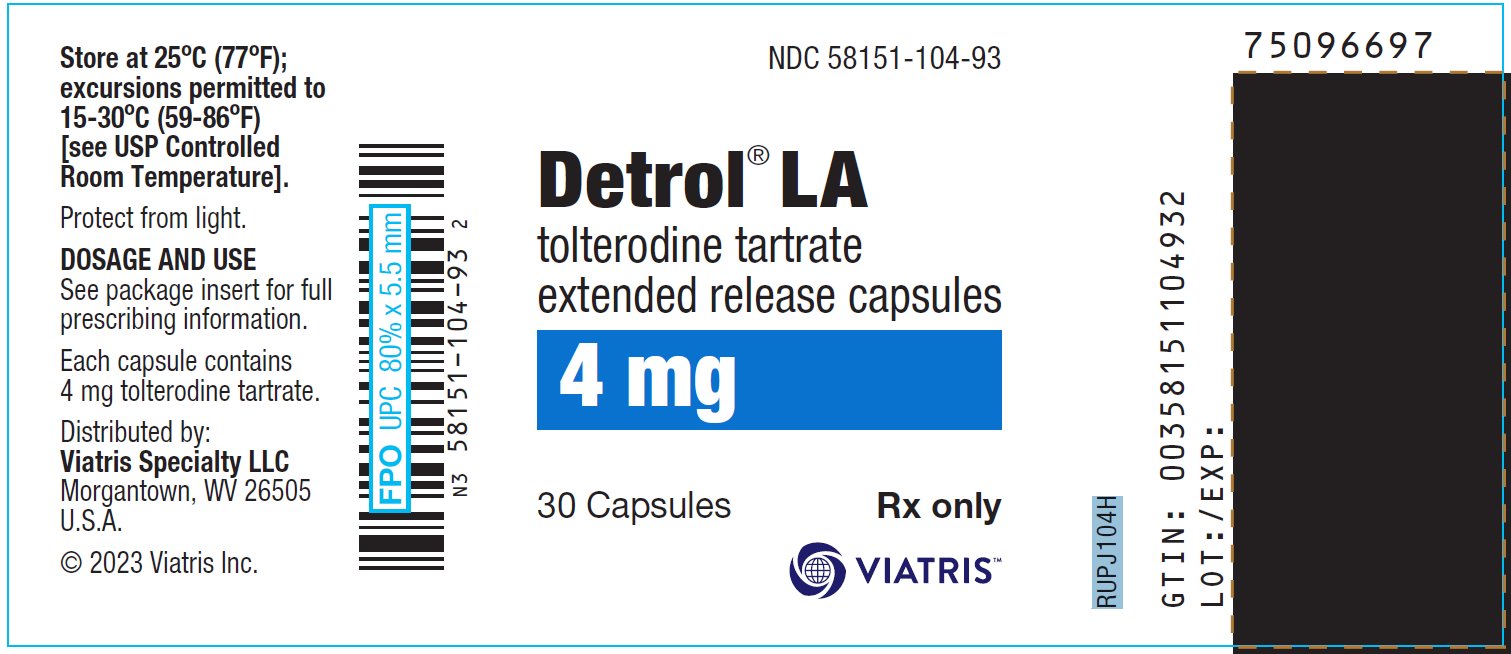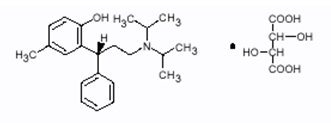 DRUG LABEL: Detrol LA
NDC: 58151-103 | Form: CAPSULE, EXTENDED RELEASE
Manufacturer: Viatris Specialty LLC
Category: prescription | Type: HUMAN PRESCRIPTION DRUG LABEL
Date: 20230315

ACTIVE INGREDIENTS: TOLTERODINE TARTRATE 2 mg/1 1
INACTIVE INGREDIENTS: ETHYLCELLULOSE, UNSPECIFIED; FD&C BLUE NO. 2; GELATIN, UNSPECIFIED; HYPROMELLOSE, UNSPECIFIED; MEDIUM-CHAIN TRIGLYCERIDES; OLEIC ACID; PROPYLENE GLYCOL; SHELLAC; DIMETHICONE; SILICON DIOXIDE; STARCH, CORN; SUCROSE; TITANIUM DIOXIDE; FERRIC OXIDE YELLOW

HIGHLIGHTS OF PRESCRIBING INFORMATION

These highlights do not include all the information needed to use Detrol® LA safely and effectively. See full prescribing information for Detrol® LA.
Detrol® LA (tolterodine tartrate extended release capsules), for oral administration
Initial U.S. Approval: December 2000

1 INDICATIONS AND USAGE

DETROL LA is an antimuscarinic indicated for the treatment of overactive bladder with symptoms of urge urinary incontinence, urgency, and frequency. (1)

2 DOSAGE AND ADMINISTRATION

- 4 mg capsules taken orally once daily with water and swallowed whole. (2.1)
- 2 mg capsules taken orally once daily with water and swallowed whole in the presence of:
  - mild to moderate hepatic impairment (Child-Pugh class A or B) (2.2)
  - severe renal impairment [Creatinine Clearance (CCr) 10‑30 mL/min] (2.2)
  - drugs that are potent CYP3A4 inhibitors. (2.2)
- DETROL LA is not recommended for use in patients with CCr <10 mL/min. (2.2)
- DETROL LA is not recommended for use in patients with severe hepatic impairment (Child-Pugh Class C). (2.2)

3 DOSAGE FORMS AND STRENGTHS

Capsules: 2 mg and 4 mg (3)

4 CONTRAINDICATIONS

DETROL LA is contraindicated in patients with urinary retention, gastric retention, or uncontrolled narrow-angle glaucoma. DETROL LA is also contraindicated in patients with known hypersensitivity to the drug or its ingredients, or to fesoterodine fumarate extended-release tablets which, like DETROL LA, are metabolized to 5-hydroxymethyl tolterodine. (4)

5 WARNINGS AND PRECAUTIONS

- Anaphylaxis and angioedema requiring hospitalization and emergency medical treatment have occurred with the first or subsequent doses of DETROL LA. (5.1)
- Urinary Retention: use caution in patients with clinically significant bladder outflow obstruction because of the risk of urinary retention. (5.2)
- Gastrointestinal Disorders: use caution in patients with gastrointestinal obstructive disorders or decreased gastrointestinal motility because of the risk of gastric retention. (5.3)
- Controlled Narrow-Angle Glaucoma: use caution in patients being treated for narrow-angle glaucoma. (5.4)
- Central Nervous System Effects: Somnolence has been reported with Detrol LA. Advise patients not to drive or operate heavy machinery until they know how Detrol LA affects them (5.5).
- Myasthenia Gravis: use caution in patients with myasthenia gravis. (5.8)
- QT Prolongation: consider observations from the thorough QT study in clinical decisions to prescribe DETROL LA to patients with a known history of QT prolongation or to patients who are taking Class IA (e.g., quinidine, procainamide) or Class III (e.g., amiodarone, sotalol) antiarrhythmic medications. (5.9)

6 ADVERSE REACTIONS

The most common adverse reactions (incidence ≥4% and >placebo) were dry mouth, headache, constipation, and abdominal pain. (6.1)

To report SUSPECTED ADVERSE REACTIONS, contact Viatris at 1-877-446-3679 (1-877-4-INFO-RX) or FDA at 1-800-FDA-1088 or www.fda.gov/medwatch.

7 DRUG INTERACTIONS

- Potent CYP3A4 Inhibitors: Coadministration may increase systemic exposure to DETROL LA. Reduce DETROL LA dose to 2 mg once daily. (7.2)
- Other Anticholinergics (antimuscarinics): Concomitant use with other anticholinergic agents may increase the frequency and/or severity of dry mouth, constipation, blurred vision, and other anticholinergic pharmacological effects. (7.6)

8 USE IN SPECIFIC POPULATIONS

- Renal Impairment: DETROL LA is not recommended for use in patients with CCr <10 mL/min. Dose adjustment in severe renal impairment (CCr: 10-30 mL/min). (8.6)
- Hepatic Impairment: Not recommended for use in severe hepatic impairment (Child Pugh Class C). Dose adjustment in mild to moderate hepatic impairment (Child Pugh Class A, B). (8.7)

FULL PRESCRIBING INFORMATION

1 INDICATIONS AND USAGE

DETROL LA Capsules is indicated for the treatment of overactive bladder with symptoms of urge urinary incontinence, urgency, and frequency [see Clinical Studies (14)].

2 DOSAGE AND ADMINISTRATION

2.1 Dosing Information

The recommended dose of DETROL LA Capsules is 4 mg once daily with water and swallowed whole. The dose may be lowered to 2 mg daily based on individual response and tolerability; however, limited efficacy data are available for DETROL LA 2 mg [see Clinical Studies (14)].

2.2 Dosage Adjustment in Specific Populations

For patients with mild to moderate hepatic impairment (Child-Pugh Class A or B) or severe renal impairment (CCr 10-30 mL/min), the recommended dose of DETROL LA is 2 mg once daily. DETROL LA is not recommended for use in patients with severe hepatic impairment (Child-Pugh Class C). Patients with CCr<10 mL/min have not been studied and use of DETROL LA in this population is not recommended [see Warnings and Precautions (5.6) and Use in Specific Populations (8.6, 8.7)].

2.3 Dosage Adjustment in Presence of Concomitant Drugs

For patients who are taking drugs that are potent inhibitors of CYP3A4 [e.g., ketoconazole, clarithromycin, ritonavir], the recommended dose of DETROL LA is 2 mg once daily [see Drug Interactions (7.2)].

3 DOSAGE FORMS AND STRENGTHS

The 2 mg capsules are blue-green with symbol and 2 printed in white ink.

The 4 mg capsules are blue with symbol and 4 printed in white ink.

4 CONTRAINDICATIONS

DETROL LA is contraindicated in patients with urinary retention, gastric retention, or uncontrolled narrow-angle glaucoma. DETROL LA is also contraindicated in patients with known hypersensitivity to the drug or its ingredients, or to fesoterodine fumarate extended-release tablets which, like DETROL LA, are metabolized to 5-hydroxymethyl tolterodine [see Warnings and Precautions (5.2, 5.3, 5.4)].

5 WARNINGS AND PRECAUTIONS

5.1 Angioedema

Anaphylaxis and angioedema requiring hospitalization and emergency medical treatment have occurred with the first or subsequent doses of DETROL LA. In the event of difficulty in breathing, upper airway obstruction, or fall in blood pressure, DETROL LA should be discontinued and appropriate therapy promptly provided.

5.2 Urinary Retention

Administer DETROL LA Capsules with caution to patients with clinically significant bladder outflow obstruction because of the risk of urinary retention [see Contraindications (4)].

5.3 Gastrointestinal Disorders

Administer DETROL LA with caution in patients with gastrointestinal obstructive disorders because of the risk of gastric retention.

DETROL LA, like other antimuscarinic drugs, may decrease gastrointestinal motility and should be used with caution in patients with conditions associated with decreased gastrointestinal motility (e.g., intestinal atony) [see Contraindications (4)].

5.4 Controlled Narrow-Angle Glaucoma

Administer DETROL LA with caution in patients being treated for narrow-angle glaucoma [see Contraindications (4)].

5.5 Central Nervous System Effects

Detrol LA is associated with anticholinergic central nervous system (CNS) effects [see Adverse Reactions (6.2)] including dizziness and somnolence [see Adverse Reactions (6.1)]. Patients should be monitored for signs of anticholinergic CNS effects, particularly after beginning treatment or increasing the dose. Advise patients not to drive or operate heavy machinery until the drug’s effects have been determined. If a patient experiences anticholinergic CNS effects, dose reduction or drug discontinuation should be considered.

5.6 Hepatic Impairment

The clearance of orally administered tolterodine immediate release was substantially lower in cirrhotic patients than in the healthy volunteers. For patients with mild to moderate hepatic impairment (Child-Pugh Class A or B), the recommended dose for DETROL LA is 2 mg once daily. DETROL LA is not recommended for use in patients with severe hepatic impairment (Child-Pugh Class C) [see Dosage and Administration (2.2) and Use in Specific Populations (8.6)].

5.7 Renal Impairment

Renal impairment can significantly alter the disposition of tolterodine and its metabolites. The dose of DETROL LA should be reduced to 2 mg once daily in patients with severe renal impairment (CCr: 10-30 mL/min). Patients with CCr<10 mL/min have not been studied and use of DETROL LA in this population is not recommended [see Dosage and Administration (2.2) and Use in Specific Populations (8.7)].

5.8 Myasthenia Gravis

Administer DETROL LA with caution in patients with myasthenia gravis, a disease characterized by decreased cholinergic activity at the neuromuscular junction.

5.9 Use in Patients with Congenital or Acquired QT Prolongation

In a study of the effect of tolterodine immediate release tablets on the QT interval [see Clinical Pharmacology (12.2)], the effect on the QT interval appeared greater for 8 mg/day (two times the therapeutic dose) compared to 4 mg/day and was more pronounced in CYP2D6 poor metabolizers (PM) than extensive metabolizers (EMs). The effect of tolterodine 8 mg/day was not as large as that observed after four days of therapeutic dosing with the active control moxifloxacin. However, the confidence intervals overlapped.

These observations should be considered in clinical decisions to prescribe DETROL LA to patients with a known history of QT prolongation or to patients who are taking Class IA (e.g., quinidine, procainamide) or Class III (e.g., amiodarone, sotalol) antiarrhythmic medications. There has been no association of Torsade de Pointes in the international post-marketing experience with DETROL or DETROL LA.

6 ADVERSE REACTIONS

Because clinical trials are conducted under widely varying conditions, adverse reaction rates observed in the clinical trials of a drug cannot be directly compared to rates in the clinical trials of another drug and may not reflect the rates observed in practice.

6.1 Clinical Trials Experience

The efficacy and safety of DETROL LA Capsules was evaluated in 1073 patients (537 assigned to DETROL LA; 536 assigned to placebo) who were treated with 2, 4, 6, or 8 mg/day for up to 15 months. These included a total of 1012 patients (505 randomized to DETROL LA 4 mg once daily and 507 randomized to placebo) enrolled in a randomized, placebo-controlled, double-blind, 12-week clinical efficacy and safety study.

Adverse events were reported in 52% (n=263) of patients receiving DETROL LA and in 49% (n=247) of patients receiving placebo. The most common adverse events reported by patients receiving DETROL LA were dry mouth, headache, constipation, and abdominal pain. Dry mouth was the most frequently reported adverse event for patients treated with DETROL LA, occurring in 23.4% of patients treated with DETROL LA and 7.7% of placebo-treated patients. Dry mouth, constipation, abnormal vision (accommodation abnormalities), urinary retention, and dry eyes are expected side effects of antimuscarinic agents. A serious adverse event was reported by 1.4% (n=7) of patients receiving DETROL LA and by 3.6% (n=18) of patients receiving placebo.

Table 1 lists the adverse events, regardless of causality, that were reported in the randomized, double-blind, placebo-controlled 12-week study at an incidence greater than placebo and in greater than or equal to 1% of patients treated with DETROL LA 4 mg once daily.

Table 1. Incidence [in nearest integer.] (%) of Adverse Events Exceeding Placebo Rate and Reported in ≥1% of Patients Treated with DETROL LA (4 mg daily) in a 12-week, Phase 3 Clinical Trial
Body System | Adverse Event | % DETROL LA; n=505 | % Placebo; n=507
Autonomic Nervous | dry mouth | 23 | 8
General | headache | 6 | 5
General | fatigue | 2 | 1
Central/Peripheral Nervous | dizziness | 2 | 1
Gastrointestinal | constipation | 6 | 4
Gastrointestinal | abdominal pain | 4 | 2
Gastrointestinal | dyspepsia | 3 | 1
Vision | xerophthalmia | 3 | 2
Vision | vision abnormal | 1 | 0
Psychiatric | somnolence | 3 | 2
Psychiatric | anxiety | 1 | 0
Respiratory | sinusitis | 2 | 1
Urinary | dysuria | 1 | 0

The frequency of discontinuation due to adverse events was highest during the first 4 weeks of treatment. Similar percentages of patients treated with DETROL LA or placebo discontinued treatment due to adverse events. Dry mouth was the most common adverse event leading to treatment discontinuation among patients receiving DETROL LA [n=12 (2.4%) vs. placebo n=6 (1.2%)].

6.2 Post-marketing Experience

The following events have been reported in association with tolterodine use in worldwide post-marketing experience:

General: anaphylaxis and angioedema; Cardiovascular: tachycardia, palpitations, peripheral edema; Gastrointestinal: diarrhea; Central/Peripheral Nervous: confusion, disorientation, memory impairment, hallucinations.

Reports of aggravation of symptoms of dementia (e.g., confusion, disorientation, delusion) have been reported after tolterodine therapy was initiated in patients taking cholinesterase inhibitors for the treatment of dementia.

Because these spontaneously reported events are from the worldwide post-marketing experience, the frequency of events and the role of tolterodine in their causation cannot be reliably determined.

7 DRUG INTERACTIONS

7.1 Potent CYP2D6 Inhibitors

Fluoxetine, a potent inhibitor of CYP2D6 activity, significantly inhibited the metabolism of tolterodine immediate release in CYP2D6 extensive metabolizers, resulting in a 4.8-fold increase in tolterodine AUC. There was a 52% decrease in Cmax and a 20% decrease in AUC of 5-hydroxymethyl tolterodine (5-HMT), the pharmacologically active metabolite of tolterodine [see Clinical Pharmacology (12.1)]. The sums of unbound serum concentrations of tolterodine and 5-HMT are only 25% higher during the interaction. No dose adjustment is required when tolterodine and fluoxetine are co-administered [see Clinical Pharmacology (12.3)].

7.2 Potent CYP3A4 Inhibitors

Ketoconazole (200 mg daily), a potent CYP3A4 inhibitor, increased the mean Cmax and AUC of tolterodine by 2- and 2.5-fold, respectively, in CYP2D6 poor metabolizers.

For patients receiving ketoconazole or other potent CYP3A4 inhibitors such as itraconazole, clarithromycin, or ritonavir, the recommended dose of DETROL LA is 2 mg once daily [see Dosage and Administration (2.2) and Clinical Pharmacology (12.3)].

7.3 Other Interactions

No clinically relevant interactions have been observed when tolterodine was co-administered with warfarin, with a combined oral contraceptive drug containing ethinyl estradiol and levonorgestrel, or with diuretics [see Clinical Pharmacology (12.3)].

7.4 Other Drugs Metabolized by Cytochrome P450 Isoenzymes

In vivo drug-interaction data show that tolterodine immediate release does not result in clinically relevant inhibition of CYP1A2, 2D6, 2C9, 2C19, or 3A4 as evidenced by lack of influence on the marker drugs caffeine, debrisoquine, S-warfarin, and omeprazole [see Clinical Pharmacology (12.3)].

7.5 Drug-Laboratory-Test Interactions

Interactions between tolterodine and laboratory tests have not been studied.

7.6 Other Anticholinergics

The concomitant use of DETROL LA with other anticholinergic (antimuscarinic) agents may increase the frequency and/or severity of dry mouth, constipation, blurred vision, somnolence, and other anticholinergic pharmacological effects.

8 USE IN SPECIFIC POPULATIONS

8.1 Pregnancy

Risk Summary

There are no available data with DETROL LA use in pregnant women to inform drug-associated risks. In animal reproduction studies, oral administration of tolterodine and its 5-HMT metabolite to pregnant mice during organogenesis did not produce adverse developmental outcomes at doses approximately 9 to 12 times the clinical exposure at a dose of 20 mg/kg/day; however, higher doses produced adverse developmental outcomes (see Data).

In the U.S. general population, the estimated background rate of major birth defects and miscarriage in clinically recognized pregnancies is 2-4% and 15-20%, respectively.

Data

Animal Data

No anomalies or malformations were observed after oral administration of tolterodine to pregnant mice during organogenesis at approximately 9-12 times the clinical exposure to the pharmacologically active components of DETROL LA (based on the AUC of tolterodine and its 5-HMT metabolite at a dose of 20 mg/kg/day). At 14-18 times the clinical exposure (doses of 30 to 40 mg/kg/day) in mice, tolterodine was embryo-lethal, caused reduced fetal weight, and increased the incidence of fetal abnormalities (cleft palate, digital abnormalities, intra‑abdominal hemorrhage, and various skeletal abnormalities, primarily reduced ossification). Pregnant rabbits administered tolterodine subcutaneously at about 0.3-2.5 times the clinical exposure (dose of 0.8 mg/kg/day) did not show any embryotoxicity or teratogenicity.

8.2 Lactation

Risk Summary

There is no information on the presence of tolterodine or its 5-HMT metabolite in human milk, the effects on the breastfed infant, or the effects on milk production. Based on limited data, tolterodine is excreted into the milk in mice in low amounts (see Data). The development and health benefits of breastfeeding should be considered along with the mother’s clinical need for DETROL LA and any potential adverse effects on the breastfed infant from DETROL LA or from the underlying maternal condition.

Animal Data

The use of radiolabeled tolterodine in pregnant mice produced milk: plasma ratios that ranged between 0.0 and 0.7.

8.4 Pediatric Use

The effectiveness of DETROL LA has not been established in pediatric patients.

Efficacy was not established in two randomized, placebo-controlled, double-blind, 12-week studies that enrolled 710 pediatric patients (486 on DETROL LA, 224 on placebo) aged 5–10 years with urinary frequency and urge incontinence. The percentage of patients with urinary tract infections was higher in patients treated with DETROL LA (6.6%) compared to patients who received placebo (4.5%). Aggressive, abnormal, and hyperactive behavior and attention disorders occurred in 2.9% of children treated with DETROL LA compared to 0.9% of children treated with placebo.

8.5 Geriatric Use

No overall differences in safety were observed between the older and younger patients treated with tolterodine.

In multiple-dose studies in which tolterodine immediate release 4 mg (2 mg bid) was administered, serum concentrations of tolterodine and of 5-HMT were similar in healthy elderly volunteers (aged 64 through 80 years) and healthy young volunteers (aged less than 40 years). In another clinical study, elderly volunteers (aged 71 through 81 years) were given tolterodine immediate release 2 or 4 mg (1 or 2 mg bid). Mean serum concentrations of tolterodine and 5-HMT in these elderly volunteers were approximately 20% and 50% higher, respectively, than concentrations reported in young healthy volunteers. However, no overall differences were observed in safety between older and younger patients on tolterodine in the Phase 3, 12-week, controlled clinical studies; therefore, no tolterodine dosage adjustment for elderly patients is recommended.

8.6 Renal Impairment

Renal impairment can significantly alter the disposition of tolterodine immediate release and its metabolites. In a study conducted in patients with creatinine clearance between 10 and 30 mL/min, tolterodine and 5-HMT levels were approximately 2–3 fold higher in patients with renal impairment than in healthy volunteers. Exposure levels of other metabolites of tolterodine (e.g., tolterodine acid, N-dealkylated tolterodine acid, N-dealkylated tolterodine, and N-dealkylated hydroxy tolterodine) were significantly higher (10–30 fold) in renally impaired patients as compared to the healthy volunteers. The recommended dose for patients with severe renal impairment (CCr: 10-30 mL/min) is DETROL LA 2 mg daily. Patients with CCr<10 mL/min have not been studied and use of DETROL LA in this population is not recommended [see Dosage and Administration (2.2) and Warnings and Precautions (5.6)]. DETROL LA has not been studied in patients with mild to moderate renal impairment [CCr 30-80 mL/min].

8.7 Hepatic Impairment

Liver impairment can significantly alter the disposition of tolterodine immediate release. In a study of tolterodine immediate release conducted in cirrhotic patients (Child-Pugh Class A and B), the elimination half-life of tolterodine immediate release was longer in cirrhotic patients (mean, 7.8 hours) than in healthy, young, and elderly volunteers (mean, 2 to 4 hours). The clearance of orally administered tolterodine immediate release was substantially lower in cirrhotic patients (1.0 ± 1.7 L/h/kg) than in the healthy volunteers (5.7 ± 3.8 L/h/kg). The recommended dose for patients with mild to moderate hepatic impairment (Child-Pugh Class A or B) is DETROL LA 2 mg once daily. DETROL LA is not recommended for use in patients with severe hepatic impairment (Child-Pugh Class C) [see Dosage and Administration (2.2) and Warnings and Precautions (5.4)].

10 OVERDOSAGE

Overdosage with DETROL LA Capsules can potentially result in severe central anticholinergic effects and should be treated accordingly.

ECG monitoring is recommended in the event of overdosage. In dogs, changes in the QT interval (slight prolongation of 10% to 20%) were observed at a suprapharmacologic dose of 4.5 mg/kg, which is about 68 times higher than the recommended human dose. In clinical trials of normal volunteers and patients, QT interval prolongation was observed with tolterodine immediate release at doses up to 8 mg (4 mg bid) and higher doses were not evaluated [see Warnings and Precautions (5.9) and Clinical Pharmacology (12.2)].

A 27-month-old child who ingested 5 to 7 tolterodine immediate release 2 mg tablets was treated with a suspension of activated charcoal and was hospitalized overnight with symptoms of dry mouth. The child fully recovered.

11 DESCRIPTION

DETROL LA Capsules contain tolterodine tartrate. The active moiety, tolterodine, is a muscarinic receptor antagonist. The chemical name of tolterodine tartrate is (R)-N,N-diisopropyl-3-(2-hydroxy-5-methylphenyl)-3-phenylpropanamine L-hydrogen tartrate. The empirical formula of tolterodine tartrate is C26H37NO7. Its structure is:

Tolterodine tartrate is a white, crystalline powder with a molecular weight of 475.6. The pKa value is 9.87 and the solubility in water is 12 mg/mL. It is soluble in methanol, slightly soluble in ethanol, and practically insoluble in toluene. The partition coefficient (Log D) between n-octanol and water is 1.83 at pH 7.3.

DETROL LA 4 mg capsule for oral administration contains 4 mg of tolterodine tartrate. Inactive ingredients are sucrose, starch, hypromellose, ethylcellulose, medium chain triglycerides, oleic acid, gelatin, and FD&C Blue #2.

DETROL LA 2 mg capsule for oral administration contains 2 mg of tolterodine tartrate, and the following inactive ingredients: sucrose, starch, hypromellose, ethylcellulose, medium chain triglycerides, oleic acid, gelatin, yellow iron oxide, and FD&C Blue #2.

Both the 2 mg and 4 mg capsule strengths are imprinted with a pharmaceutical grade printing ink that contains shellac glaze, titanium dioxide, propylene glycol, and simethicone.

12 CLINICAL PHARMACOLOGY

12.1 Mechanism of Action

Tolterodine acts as a competitive antagonist of acetylcholine at postganglionic muscarinic receptors. Both urinary bladder contraction and salivation are mediated via cholinergic muscarinic receptors.

After oral administration, tolterodine is metabolized in the liver, resulting in the formation of 5-hydroxymethyl tolterodine (5-HMT), the major pharmacologically active metabolite. 5-HMT, which exhibits an antimuscarinic activity similar to that of tolterodine, contributes significantly to the therapeutic effect. Both tolterodine and 5-HMT exhibit a high specificity for muscarinic receptors, since both show negligible activity or affinity for other neurotransmitter receptors and other potential cellular targets, such as calcium channels.

12.2 Pharmacodynamics

Tolterodine has a pronounced effect on bladder function. Effects on urodynamic parameters before and 1 and 5 hours after a single 6.4 mg dose of tolterodine immediate release were determined in healthy volunteers. The main effects of tolterodine at 1 and 5 hours were an increase in residual urine, reflecting an incomplete emptying of the bladder, and a decrease in detrusor pressure. These findings are consistent with an antimuscarinic action on the lower urinary tract.

Cardiac Electrophysiology

The effect of 2 mg BID and 4 mg BID of DETROL immediate release (tolterodine IR) tablets on the QT interval was evaluated in a 4-way crossover, double-blind, placebo- and active-controlled (moxifloxacin 400 mg QD) study in healthy male (N=25) and female (N=23) volunteers aged 18–55 years. Study subjects [approximately equal representation of CYP2D6 extensive metabolizers (EMs) and poor metabolizers (PMs)] completed sequential 4-day periods of dosing with moxifloxacin 400 mg QD, tolterodine 2 mg BID, tolterodine 4 mg BID, and placebo. The 4 mg BID dose of tolterodine IR (two times the highest recommended dose) was chosen because this dose results in tolterodine exposure similar to that observed upon coadministration of tolterodine 2 mg BID with potent CYP3A4 inhibitors in patients who are CYP2D6 poor metabolizers [see Drug Interactions (7.2)]. QT interval was measured over a 12-hour period following dosing, including the time of peak plasma concentration (Tmax) of tolterodine and at steady state (Day 4 of dosing).

Table 2 summarizes the mean change from baseline to steady state in corrected QT interval (QTc) relative to placebo at the time of peak tolterodine (1 hour) and moxifloxacin (2 hour) concentrations. Both Fridericia’s (QTcF) and a population-specific (QTcP) method were used to correct QT interval for heart rate. No single QT correction method is known to be more valid than others. QT interval was measured manually and by machine, and data from both are presented. The mean increase of heart rate associated with a 4 mg/day dose of tolterodine in this study was 2.0 beats/minute and 6.3 beats/minute with 8 mg/day tolterodine. The change in heart rate with moxifloxacin was 0.5 beats/minute.

Table 2. Mean (CI) change in QTc from baseline to steady state (Day 4 of dosing) at Tmax (relative to placebo)
Drug/Dose | N | QTc F; (msec) (manual) | QTc F; (msec); (machine) | QTc P; (msec); (manual) | QTc P; (msec); (machine)
Tolterodine; 2 mg BID [At Tmax of 1 hr; 95% Confidence Interval.] | 48 | 5.01; (0.28, 9.74) | 1.16; (-2.99, 5.30) | 4.45; (-0.37, 9.26) | 2.00; (-1.81, 5.81)
Tolterodine; 4 mg BID | 48 | 11.84; (7.11, 16.58) | 5.63; (1.48, 9.77) | 10.31; (5.49, 15.12) | 8.34; (4.53, 12.15)
Moxifloxacin 400 mg QD [At Tmax of 2 hr; 90% Confidence Interval.] | 45 | 19.26 [The effect on QT interval with 4 days of moxifloxacin dosing in this QT trial may be greater than typically observed in QT trials of other drugs.]; (15.49, 23.03) | 8.90; (4.77, 13.03) | 19.10; (15.32, 22.89) | 9.29; (5.34, 13.24)

The reason for the difference between machine and manual read of QT interval is unclear.

The QT effect of tolterodine immediate release tablets appeared greater for 8 mg/day (two times the therapeutic dose) compared to 4 mg/day. The effect of tolterodine 8 mg/day was not as large as that observed after four days of therapeutic dosing with the active control moxifloxacin. However, the confidence intervals overlapped.

Tolterodine’s effect on QT interval was found to correlate with plasma concentration of tolterodine. There appeared to be a greater QTc interval increase in CYP2D6 poor metabolizers than in CYP2D6 extensive metabolizers after tolterodine treatment in this study.

This study was not designed to make direct statistical comparisons between drugs or dose levels. There has been no association of Torsade de Pointes in the international post-marketing experience with DETROL or DETROL LA [see Warnings and Precautions (5.7)].

12.3 Pharmacokinetics

Absorption

In a study with ^14C-tolterodine solution in healthy volunteers who received a 5 mg oral dose, at least 77% of the radiolabeled dose was absorbed. Cmax and area under the concentration-time curve (AUC) determined after dosage of tolterodine immediate release are dose-proportional over the range of 1 to 4 mg. Based on the sum of unbound serum concentrations of tolterodine and 5-HMT (“active moiety”), the AUC of tolterodine extended release 4 mg daily is equivalent to tolterodine immediate release 4 mg (2 mg bid). Cmax and Cmin levels of tolterodine extended release are about 75% and 150% of tolterodine immediate release, respectively. Maximum serum concentrations of tolterodine extended release are observed 2 to 6 hours after dose administration.

Effect of Food

There is no effect of food on the pharmacokinetics of tolterodine extended release.

Distribution

Tolterodine is highly bound to plasma proteins, primarily α1-acid glycoprotein. Unbound concentrations of tolterodine average 3.7% ± 0.13% over the concentration range achieved in clinical studies. 5-HMT is not extensively protein bound, with unbound fraction concentrations averaging 36% ± 4.0%. The blood to serum ratio of tolterodine and 5-HMT averages 0.6 and 0.8, respectively, indicating that these compounds do not distribute extensively into erythrocytes. The volume of distribution of tolterodine following administration of a 1.28 mg intravenous dose is 113 ± 26.7 L.

Metabolism

Tolterodine is extensively metabolized by the liver following oral dosing. The primary metabolic route involves the oxidation of the 5-methyl group and is mediated by the cytochrome P450 2D6 (CYP2D6) and leads to the formation of a pharmacologically active metabolite, 5-HMT. Further metabolism leads to formation of the 5-carboxylic acid and N-dealkylated 5-carboxylic acid metabolites, which account for 51% ± 14% and 29% ± 6.3% of the metabolites recovered in the urine, respectively.

Variability in Metabolism

A subset of individuals (approximately 7% of Caucasians and approximately 2% of African Americans) are poor metabolizers for CYP2D6, the enzyme responsible for the formation of 5-HMT from tolterodine. The identified pathway of metabolism for these individuals (“poor metabolizers”) is dealkylation via cytochrome P450 3A4 (CYP3A4) to N-dealkylated tolterodine. The remainder of the population is referred to as “extensive metabolizers.” Pharmacokinetic studies revealed that tolterodine is metabolized at a slower rate in poor metabolizers than in extensive metabolizers; this results in significantly higher serum concentrations of tolterodine and in negligible concentrations of 5-HMT.

Excretion

Following administration of a 5 mg oral dose of ^14C-tolterodine solution to healthy volunteers, 77% of radioactivity was recovered in urine and 17% was recovered in feces in 7 days. Less than 1% (< 2.5% in poor metabolizers) of the dose was recovered as intact tolterodine, and 5% to 14% (<1% in poor metabolizers) was recovered as 5-HMT.

A summary of mean (± standard deviation) pharmacokinetic parameters of tolterodine extended release and 5-HMT in extensive (EM) and poor (PM) metabolizers is provided in Table 3. These data were obtained following single and multiple doses of tolterodine extended release administered daily to 17 healthy male volunteers (13 EM, 4 PM).

Table 3. Summary of Mean (±SD) Pharmacokinetic Parameters of Tolterodine Extended Release and its Active Metabolite (5-Hydroxymethyl Tolterodine) in Healthy Volunteers
 | Tolterodine |  |  |  |  | 5-Hydroxymethyl Tolterodine
 | tmax [Data presented as median (range).]; (h) |  | Cmax (µg/L) | Cavg; (µg/L) | t½; (h) | tmax; (h) | Cmax; (µg/L) | Cavg; (µg/L) | t½; (h)
Single dose; 4 mg [Parameter dose-normalized from 8 to 4 mg for the single-dose data.]; EM | 4 (2–6) |  | 1.3 (0.8) | 0.8 (0.57) | 8.4 (3.2) | 4 (3–6) | 1.6 (0.5) | 1.0 (0.32) | 8.8 (5.9)
Multiple; dose 4 mg; EM; PM | 4 (2–6); 4 (3–6) |  | 3.4 (4.9); 19 (16) | 1.7 (2.8); 13 (11) | 6.9 (3.5); 18 (16) | 4 (2–6); [= not applicable.] | 2.7 (0.90) | 1.4 (0.6) | 9.9 (4.0)
Cmax = Maximum serum concentration; tmax = Time of occurrence of Cmax;
Cavg = Average serum concentration; t1/2 = Terminal elimination half-life.

Drug Interactions

Potent CYP2D6 Inhibitors

Fluoxetine is a selective serotonin reuptake inhibitor and a potent inhibitor of CYP2D6 activity. In a study to assess the effect of fluoxetine on the pharmacokinetics of tolterodine immediate release and its metabolites, it was observed that fluoxetine significantly inhibited the metabolism of tolterodine immediate release in extensive metabolizers, resulting in a 4.8-fold increase in tolterodine AUC. There was a 52% decrease in Cmax and a 20% decrease in AUC of 5-hydroxymethyl tolterodine (5-HMT, the pharmacologically active metabolite of tolterodine). Fluoxetine thus alters the pharmacokinetics in patients who would otherwise be CYP2D6 extensive metabolizers of tolterodine immediate release to resemble the pharmacokinetic profile in poor metabolizers. The sums of unbound serum concentrations of tolterodine immediate release and 5-HMT are only 25% higher during the interaction. No dose adjustment is required when tolterodine and fluoxetine are co-administered.

Potent CYP3A4 Inhibitors

The effect of a 200 mg daily dose of ketoconazole on the pharmacokinetics of tolterodine immediate release was studied in 8 healthy volunteers, all of whom were CYP2D6 poor metabolizers. In the presence of ketoconazole, the mean Cmax and AUC of tolterodine increased by 2- and 2.5-fold, respectively. Based on these findings, other potent CYP3A4 inhibitors may also lead to increases of tolterodine plasma concentrations.

For patients receiving ketoconazole or other potent CYP3A4 inhibitors such as itraconazole, miconazole, clarithromycin, ritonavir, the recommended dose of DETROL LA is 2 mg daily [see Dosage and Administration (2.3)].

Warfarin

In healthy volunteers, coadministration of tolterodine immediate release 4 mg (2 mg bid) for 7 days and a single dose of warfarin 25 mg on day 4 had no effect on prothrombin time, Factor VII suppression, or on the pharmacokinetics of warfarin.

Oral Contraceptives

Tolterodine immediate release 4 mg (2 mg bid) had no effect on the pharmacokinetics of an oral contraceptive (ethinyl estradiol 30 µg/levonorgestrel 150 µg) as evidenced by the monitoring of ethinyl estradiol and levonorgestrel over a 2-month period in healthy female volunteers.

Diuretics

Coadministration of tolterodine immediate release up to 8 mg (4 mg bid) for up to 12 weeks with diuretic agents, such as indapamide, hydrochlorothiazide, triamterene, bendroflumethiazide, chlorothiazide, methylchlorothiazide, or furosemide, did not cause any adverse electrocardiographic (ECG) effects.

Effect of Tolterodine on Other Drugs Metabolized by Cytochrome P450 Enzymes

Tolterodine immediate release does not cause clinically significant interactions with other drugs metabolized by the major drug-metabolizing CYP enzymes. In vivo drug-interaction data show that tolterodine immediate release does not result in clinically relevant inhibition of CYP1A2, 2D6, 2C9, 2C19, or 3A4 as evidenced by lack of influence on the marker drugs caffeine, debrisoquine, S-warfarin, and omeprazole. In vitro data show that tolterodine immediate release is a competitive inhibitor of CYP2D6 at high concentrations (Ki 1.05 µM), while tolterodine immediate release as well as the 5-HMT are devoid of any significant inhibitory potential regarding the other isoenzymes.

13 NONCLINICAL TOXICOLOGY

13.1 Carcinogenesis, Mutagenesis, Impairment of Fertility

Carcinogenicity studies with tolterodine were conducted in mice and rats. At the maximum tolerated dose in mice (30 mg/kg/day), female rats (20 mg/kg/day), and male rats (30 mg/kg/day), exposure margins were approximately 6-9 times, 7 times, and 11 times the clinical exposure to the pharmacologically active components of DETROL LA (based on AUC of tolterodine and its 5-HMT metabolite). At these exposure margins, no increase in tumors was found in either mice or rats.

No mutagenic or genotoxic effects of tolterodine were detected in a battery of in vitro tests, including bacterial mutation assays (Ames test) in 4 strains of Salmonella typhimurium and in 2 strains of Escherichia coli, a gene mutation assay in L5178Y mouse lymphoma cells, and chromosomal aberration tests in human lymphocytes. Tolterodine was also negative in vivo in the bone marrow micronucleus test in the mouse.

In female mice treated for 2 weeks before mating and during gestation with 20 mg/kg/day (about 9-12 times the clinical exposure via AUC), neither effects on reproductive performance or fertility were seen. In male mice, a dose of 30 mg/kg/day did not induce any adverse effects on fertility.

14 CLINICAL STUDIES

DETROL LA Capsules 2 mg were evaluated in 29 patients in a Phase 2 dose-effect study. DETROL LA 4 mg was evaluated for the treatment of overactive bladder with symptoms of urge urinary incontinence and frequency in a randomized, placebo-controlled, multicenter, double-blind, Phase 3, 12-week study. A total of 507 patients received DETROL LA 4 mg once daily in the morning and 508 received placebo. The majority of patients were Caucasian (95%) and female (81%), with a mean age of 61 years (range, 20 to 93 years). In the study, 642 patients (42%) were 65 to 93 years of age. The study included patients known to be responsive to tolterodine immediate release and other anticholinergic medications, however, 47% of patients never received prior pharmacotherapy for overactive bladder. At study entry, 97% of patients had at least 5 urge incontinence episodes per week and 91% of patients had 8 or more micturitions per day.

The primary efficacy assessment was change in mean number of incontinence episodes per week at week 12 from baseline. Secondary efficacy measures included change in mean number of micturitions per day and mean volume voided per micturition at week 12 from baseline.

Patients treated with DETROL LA experienced a statistically significant decrease in number of urinary incontinence per week from baseline to last assessment (week 12) compared with placebo as well as a decrease in the average daily urinary frequency and an increase in the average urine volume per void.

Mean change from baseline in weekly incontinence episodes, urinary frequency, and volume voided between placebo and DETROL LA are summarized in Table 4.

Table 4. 95% Confidence Intervals (CI) for the Difference between DETROL LA (4 mg daily) and Placebo for Mean Change at Week 12 from Baseline [Intent-to-treat analysis.]
 | DETROL LA; (n=507) | Placebo; (n=508) [1 to 2 patients missing in placebo group for each efficacy parameter.] | Treatment; Difference, vs. Placebo; (95% Cl)
Number of incontinence episodes/week; Mean Baseline; Mean Change from Baseline | 22.1; –11.8 (SD 17.8) | 23.3; –6.9 (SD 15.4) | -4.8 [The difference between DETROL LA and placebo was statistically significant.]; (–6.9, –2.8)
Number of micturitions/day; Mean Baseline; Mean Change from Baseline | 10.9; –1.8 (SD 3.4) | 11.3; –1.2 (SD 2.9) | -0.6; (–1.0, –0.2)
Volume voided per micturition (mL); Mean Baseline; Mean Change from Baseline | 141; 34 (SD 51) | 136; 14 (SD 41) | 20; (14, 26)
SD = Standard Deviation.

16 HOW SUPPLIED/STORAGE AND HANDLING

DETROL LA Capsules are supplied as follows:

Bottles of 30 |  | Bottles of 500
2 mg Capsules | NDC 58151-103-93 | 2 mg Capsules | NDC 58151-103-05
4 mg Capsules | NDC 58151-104-93 | 4 mg Capsules | NDC 58151-104-05
Bottles of 90
2 mg Capsules | NDC 58151-103-77
4 mg Capsules | NDC 58151-104-77

Store at 20°–25°C (68°–77°F); excursions permitted to 15–30°C (59–86°F) [see USP Controlled Room Temperature]. Protect from light.

17 PATIENT COUNSELING INFORMATION

Advise the patient to read the FDA-approved patient labeling (Patient Information).

Antimuscarinic Effects

Inform patients that antimuscarinic agents such as DETROL LA may have side effects including blurred vision, dizziness, or drowsiness. Advise patients not to drive, operate machinery, or do other potentially dangerous activities until they know how DETROL LA affects them.

Distributed by:
Viatris Specialty LLC
Morgantown, WV 26505 U.S.A.

© 2023 Viatris Inc.

DETROL is a registered trademark of Viatris Specialty LLC, a Viatris Company.

UPJ:DTRLLAC:R1

PATIENT INFORMATION

DETROL® LA (DE-trol el-ay)
(tolterodine tartrate extended release capsules)

Read the Patient Information that comes with DETROL LA before you start using it and each time you get a refill. There may be new information. This leaflet does not take the place of talking with your doctor about your condition or your treatment. Only your doctor can determine if treatment with DETROL LA is right for you.

What is DETROL LA?

DETROL LA is a prescription medicine for adults used to treat the following symptoms due to a condition called overactive bladder:

- Having a strong need to urinate with leaking or wetting accidents (urge urinary incontinence).
- Having a strong need to urinate right away (urgency).
- Having to urinate often (frequency).

DETROL LA did not help the symptoms of overactive bladder when studied in children.

What is overactive bladder?

Overactive bladder happens when you cannot control your bladder muscle. When the muscle contracts too often or cannot be controlled, you get symptoms of overactive bladder, which are leakage of urine (urge urinary incontinence), needing to urinate right away (urgency), and needing to urinate often (frequency).

Who should not take DETROL LA?

Do not take DETROL LA if:

- You have trouble emptying your bladder (also called “urinary retention”).
- Your stomach empties slowly (also called “gastric retention”).
- You have an eye problem called “uncontrolled narrow-angle glaucoma”.
- You are allergic to DETROL LA or to any of its ingredients. See the end of this leaflet for a complete list of ingredients.
- You are allergic to TOVIAZ®, which contains fesoterodine.

What should I tell my doctor before starting DETROL LA?

Before starting DETROL LA, tell your doctor about all of your medical conditions, including if you:

- Have any stomach or intestinal problems.
- Have trouble emptying your bladder or you have a weak urine stream.
- Have an eye problem called narrow-angle glaucoma.
- Have liver problems.
- Have kidney problems.
- Have a condition called myasthenia gravis.
- Or any family members have a rare heart condition called QT prolongation (long QT syndrome).
- Are pregnant or trying to become pregnant. It is not known if DETROL LA could harm your unborn baby.
- Are breastfeeding. It is not known if DETROL LA passes into your milk and if it can harm your child.

Tell your doctor about all the medicines you take, including prescription and non-prescription medicines, vitamins, and herbal supplements. Other drugs can affect how your body handles DETROL LA. Your doctor may use a lower dose of DETROL LA if you are taking:

- Certain medicines for fungus or yeast infections such as Nizoral® (ketoconazole), Sporanox® (itraconazole), or Monistat® (miconazole).
- Certain medicines for bacteria infections such as Biaxin® (clarithromycin).
- Certain medicines for treatment of HIV infection such as Norvir® (ritonavir), Invirase® (saquinavir), Reyataz® (atazanavir).
- Sandimmune® (cyclosporine) or Velban® (vinblastine).

Know the medicines you take. Keep a list of them with you to show your doctor or pharmacist each time you get a new medicine.

How should I take DETROL LA?

- Take DETROL LA exactly as prescribed. Your doctor will prescribe the dose that is right for you. Do not change your dose unless told to do so by your doctor.
- Take DETROL LA capsules once a day with liquid. Swallow the whole capsule. Tell your doctor if you cannot swallow a capsule.
- DETROL LA can be taken with or without food.
- Take DETROL LA the same time each day.
- If you miss a dose of DETROL LA, begin taking DETROL LA again the next day. Do not take 2 doses of DETROL LA in the same day.
- If you took more than your prescribed dose of DETROL LA, call your doctor or poison control center, or go to the hospital emergency room.

What are possible side effects of DETROL LA?

DETROL LA may cause allergic reactions that may be serious. Symptoms of a serious allergic reaction may include swelling of the face, lips, throat, or tongue. If you experience these symptoms, you should stop taking DETROL LA and get emergency medical help right away.

The most common side effects with DETROL LA are:

- Dry mouth

- Constipation

- Headache

- Stomach pain

Medicines like DETROL LA can cause blurred vision, dizziness, and drowsiness.

Do not drive, operate machinery, or do other dangerous activities until you know how DETROL LA affects you.

Call your doctor for medical advice about side effects. You may report side effects to the FDA at 1-800-FDA-1088.

These are not all the side effects with DETROL LA. For a complete list, ask your doctor or pharmacist.

How do I store DETROL LA?

- Store DETROL LA at room temperature, 68° - 77°F (20° - 25°C); brief periods permitted between 59° - 86°F (15° - 30°C). Protect from light. Keep in a dry place.
- Keep DETROL LA and all medicines out of the reach of children.

General Information about DETROL LA

Medicines are sometimes prescribed for conditions that are not in the patient information leaflet. Only use DETROL LA the way your doctor tells you. Do not share it with other people even if they have the same symptoms you have. It may harm them.

This leaflet summarizes the most important information about DETROL LA. If you would like more information, talk with your doctor. You can ask your doctor or pharmacist for information about DETROL LA that is written for health professionals. You can also call Viatris at 1-877-446-3679 (1-877-4-INFO-RX).

What are the ingredients in DETROL LA?

Active ingredients: tolterodine tartrate

Inactive ingredients: sucrose, starch, hypromellose, ethylcellulose, medium chain triglycerides, oleic acid, gelatin, and FD&C Blue #2. 2 mg capsule also contains yellow iron oxide. Capsules have pharmaceutical grade printing ink that contains shellac glaze, titanium dioxide, propylene glycol, and simethicone.

Distributed by:
Viatris Specialty LLC
Morgantown, WV 26505 U.S.A.

© 2023 Viatris Inc.

DETROL is a registered trademark of Viatris Specialty LLC, a Viatris Company.

The brands listed are trademarks of their respective owners.

UPJ:PL:DTRLLAC:R1

Revised: 3/2023

PRINCIPAL DISPLAY PANEL – 2 mg

NDC 58151-103-93

Detrol® LA

tolterodine tartrate
extended release capsules

2 mg

30 Capsules Rx only

VIATRIS™

Store at 25ºC (77ºF);
excursions permitted to
15-30ºC (59-86ºF)
[see USP Controlled
Room Temperature].

Protect from light.

DOSAGE AND USE
See package insert for full
prescribing information.

Each capsule contains
2 mg tolterodine tartrate.

Distributed by:
Viatris Specialty LLC
Morgantown, WV 26505
U.S.A.

© 2023 Viatris Inc.

RUPJ103H

PRINCIPAL DISPLAY PANEL – 4 mg

NDC 58151-104-93

Detrol® LA

tolterodine tartrate
extended release capsules

4 mg

30 Capsules Rx only

VIATRIS™

Store at 25ºC (77ºF);
excursions permitted to
15-30ºC (59-86ºF)
[see USP Controlled
Room Temperature].

Protect from light.

DOSAGE AND USE
See package insert for full
prescribing information.

Each capsule contains
4 mg tolterodine tartrate.

Distributed by:
Viatris Specialty LLC
Morgantown, WV 26505
U.S.A.

© 2023 Viatris Inc.

RUPJ104H